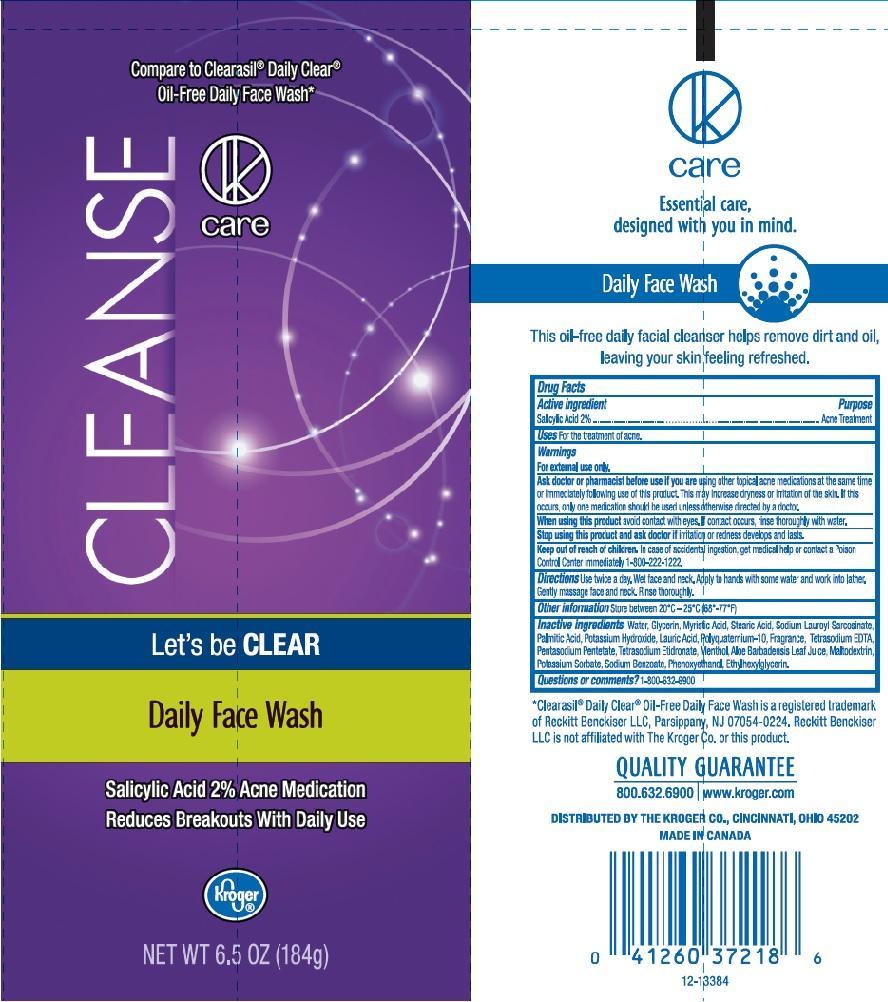 DRUG LABEL: KROGER
NDC: 30142-729 | Form: LIQUID
Manufacturer: THE KROGER COMPANY
Category: otc | Type: HUMAN OTC DRUG LABEL
Date: 20140924

ACTIVE INGREDIENTS: SALICYLIC ACID 20 mg/1 mL
INACTIVE INGREDIENTS: WATER; GLYCERIN; MYRISTIC ACID; STEARIC ACID; SODIUM LAUROYL SARCOSINATE; PALMITIC ACID; POTASSIUM HYDROXIDE; LAURIC ACID; POLYQUATERNIUM-10 (400 CPS AT 2%); EDETATE SODIUM; PENTASODIUM PENTETATE; ETIDRONATE TETRASODIUM; MENTHOL; ALOE VERA LEAF; MALTODEXTRIN; POTASSIUM SORBATE; SODIUM BENZOATE; PHENOXYETHANOL; ETHYLHEXYLGLYCERIN

DRUG FACTS

ACTIVE INGREDIENT

SALICYLIC ACID 2%

PURPOSE

ACNE TREATMENT

USES

FOR THE TREATMENT OF ACNE

WARNINGS

FOR EXTERNAL USE ONLY

ASK DOCTOR OR PHARMACIST BEFORE USE IF YOU ARE

USING OTHER TOPICAL ACNE MEDICATIONS AT THE SAME TIME OR IMMEDIATELY FOLLOWING USE OF THIS PRODUCT. THIS MAY INCREASE DRYNESS OR IRRITATION OF THE SKIN. IF THIS OCCURS, ONLY ONE MEDICATION SHOULD BE USED UNLESS OTHERWISE DIRECTED BY A DOCTOR

WHEN USING THIS PRODUCT

AVOID CONTACT WITH EYES. IF CONTACT OCCURS, RINSE THOROUGHLY WITH WATER

STOP USE

IRRITATION OR REDNESS DEVELOPS AND LASTS

KEEP OUT OF REACH OF CHILDREN

IN CASE OF ACCIDENTAL INGESTION, GET MEDICAL HELP OR CONTACT A POISON CONTROL CENTER IMMEDIATELY 1-800-222-1222

DIRECTIONS

USE TWICE A DAY. WET FACE AND NECK. APPLY TO HANDS WITH SOME WATER AND WORK INTO LATHER. GENTLY MASSAGE FACE AND NECK. RINSE THOROUGHLY

OTHER INFORMATION

STORE BETWEEN 20°C - 25°C (68°F - 77°F)

INACTIVE INGREDIENTS

WATER, GLYCEIRN, MYRISTIC ACID, STEARIC ACID, SODIUM LAUROYL SARCOSINATE, PALMITIC ACID, POTASSIUM HYDROXIDE, LAURIC ACID, POLYQUATERNIUM-10, FRAGRANCE, TETRASODIUM EDTA, PENTASODIUM PENTETATE, TETRASODIUM ETIDRONATE, MENTHOL, ALOE BARBADENSIS LEAF JUICE, MALTODEXTRIN, POTASSIUM SORBATE, SODIUM BENZOATE, PHENOXYETHANOL, ETHYLHEXYLGLYCERIN

QUESTIONS OR COMMENTS?

1-800-632-6900